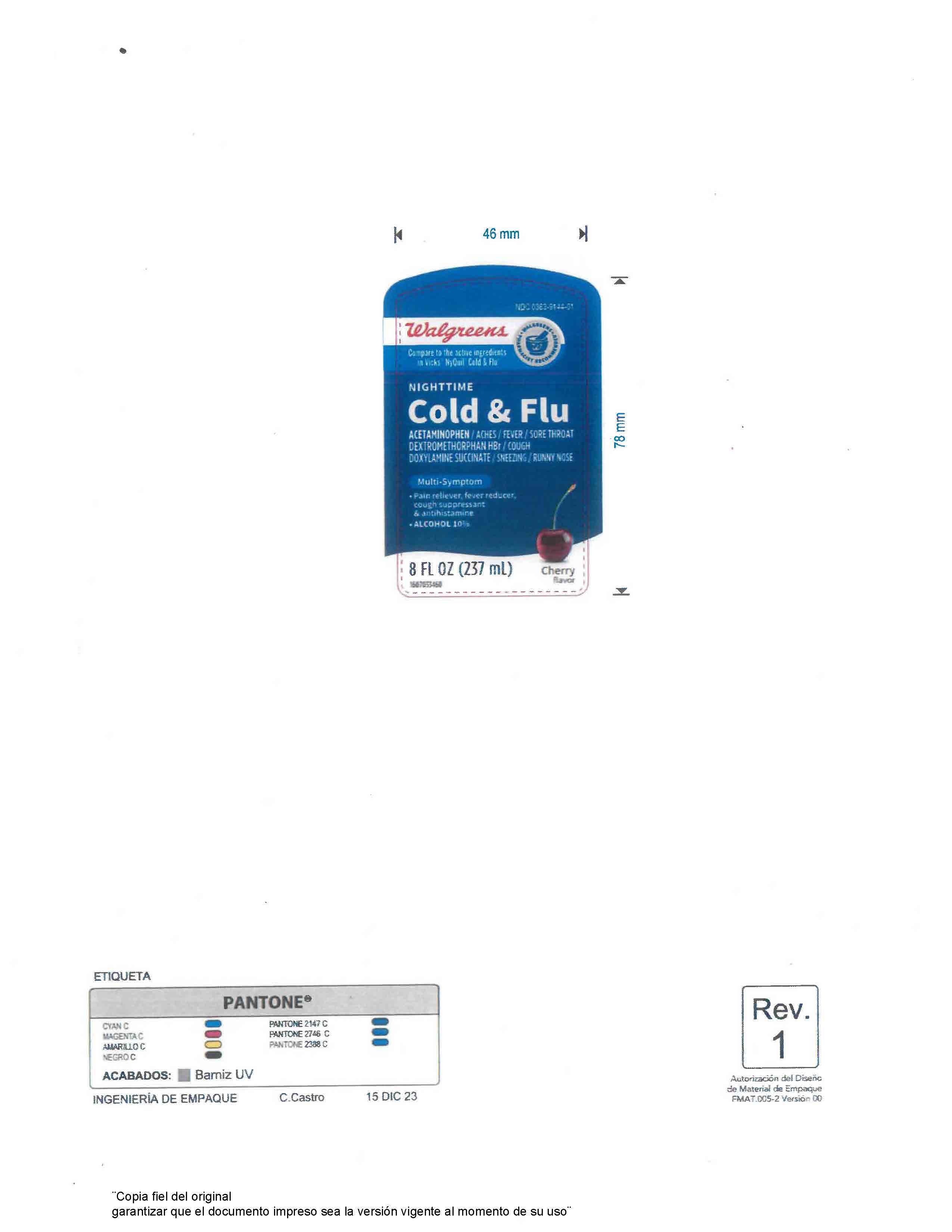 DRUG LABEL: NIGHTTIME COLD AND FLU CHERRY
NDC: 0363-9144 | Form: LIQUID
Manufacturer: Walgreen Company
Category: otc | Type: HUMAN OTC DRUG LABEL
Date: 20260126

ACTIVE INGREDIENTS: DEXTROMETHORPHAN HYDROBROMIDE 0.02 g/237 mL; ACETAMINOPHEN 0.65 g/237 mL; DOXYLAMINE SUCCINATE 0.0125 g/237 mL; PHENYLEPHRINE 0.01 g/237 mL
INACTIVE INGREDIENTS: GLYCERIN 0.03 g/237 mL

Directions

take only as directed
only use the dose cup provided
do not exceed 4 doses per 24 hrs

adults & children 12 yrs & over

30 mL every 6 hrs

children 4 to under 12 yrs

ask a doctor

children under 4 yrs

do not use

Warnings

Liver warning: This product contains acetaminophen. Severe liver damage may occur if you take

more than 4 doses in 24 hrs, which is the maximum daily amount for this product
with other drugs containing acetaminophen
3 or more alcoholic drinks every day while using this product

Allergy Alert: Acetaminophen may cause severe skin reactions.

Symptoms may include:

skin reddening
blisters
rash

If skin reaction occurs, stop use and seek medical help right away

Sore throat warning: If sore throat is severe, persist for more than 2 days, is accompanied or followed by fever, headache, rash, nausea, or vomiting, consult a doctor promptly.

INACTIVE INGREDIENT

Inactive ingredients alcohol, citric acid, D&C Yellow No. 10, FD&C Blue No.1, flavor, glycerin, propylene glycol, purified water, saccharin sodium, sodium benzoate, sodium citrate, sorbitol, sucralose

Uses

temporarily relieves common cold/flu symptoms:

cough due to minor throat & bronchial irritation
sore throat
headache
minor aches & pains
fever

runny nose and sneezing

KEEP OUT OF REACH OF CHILDREN

If pregnant or breast-feeding, ask a health professional before use. Keep out of reach of children. In case of overdose, get medical help or contact a Poison Control Center right away. Quick medical attention is critical for adults as well as for children even if you do not notice any signs or symptoms

Uses

temporarily relieves common cold/flu symptoms:

cough due to minor throat & bronchial irritation
sore throat
headache
minor aches & pains
fever

runny nose and sneezing